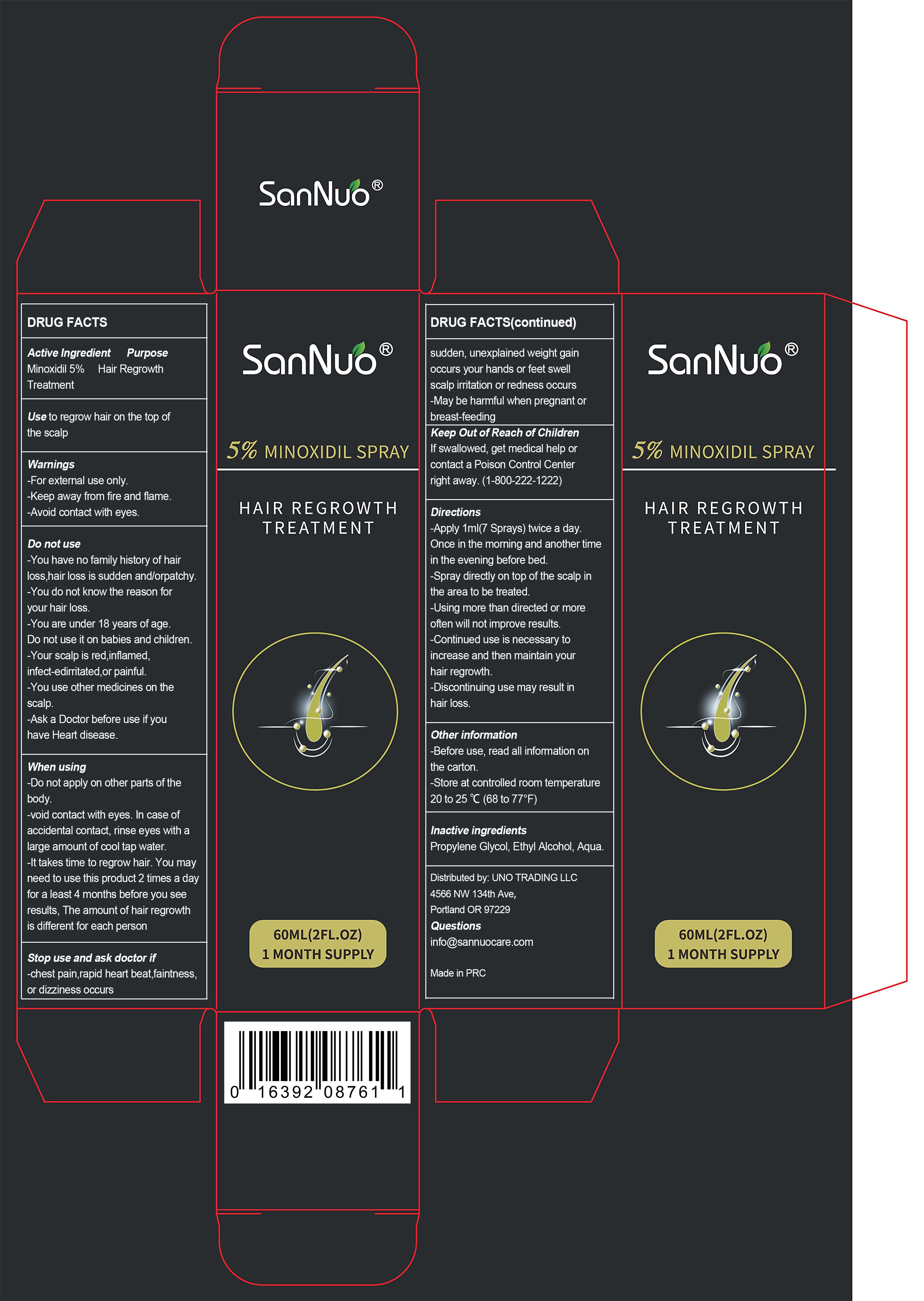 DRUG LABEL: SANNUO 5% Minoxidil Hair Growth Treatment
NDC: 83648-003 | Form: SPRAY
Manufacturer: Shenzhen Baixingchen Technology Co., Ltd.
Category: otc | Type: HUMAN OTC DRUG LABEL
Date: 20240424

ACTIVE INGREDIENTS: MINOXIDIL 5 g/10 mL
INACTIVE INGREDIENTS: WATER; PROPYLENE GLYCOL; ALCOHOL

ACTIVE INGREDIENT

Minoxidil 5%

Ask a Doctor before use if you
have Heart disease.

Warnings
-For external use only.
-Keep away from fire and flame.
-Avoid contact with eyes.

Do not use
-You have no family history of hair loss,hair loss is sudden and/orpatchy.
-You do not know the reason for your hair loss.
-You are under 18 years of age.
Do not use it on babies and children.
-Your scalp is red,inflamed, infect-edirritated,or painful.
-You use other medicines on the scalp.

When using
-Do not apply on other parts of the body.
-void contact with eyes. In case of accidental contact, rinse eyes with a large amount of cool tap water.
-It takes time to regrow hair. You may need to use this product 2 times a day for a least 4 months before you see results, The amount of hair regrowth is different for each person

Stop use and ask doctor if
-chest pain,rapid heart beat,faintness,or dizziness occurs sudden, unexplained weight gain occurs your hands or feet swell scalp irritation or redness occurs
-May be harmful when pregnant or breast-feeding

Keep Out of Reach of Children
If swallowed, get medical help or contact a Poison Control Center right away. (1-800-222-1222)

PURPOSE

Hair Regrowth Treatment

Other information
-Before use, read all information on the carton.
-Store at controlled room temperature 20 to 25 ℃ (68 to 77°F)

Directions
-Apply 1ml (7 Sprays) twice a day.
Once in the morning and another time in the evening before bed.
-Spray directly on top of the scalp in the area to be treated.
-Using more than directed or more often will not improve results.
-Continued use is necessary to increase and then maintain your hair regrowth.
-Discontinuing use may result in hair loss.

Inactive ingredients
Propylene Glycol, Ethyl Alcohol, Aqua.

INDICATIONS AND USAGE

Use to regrow hair on the top of the scalp.